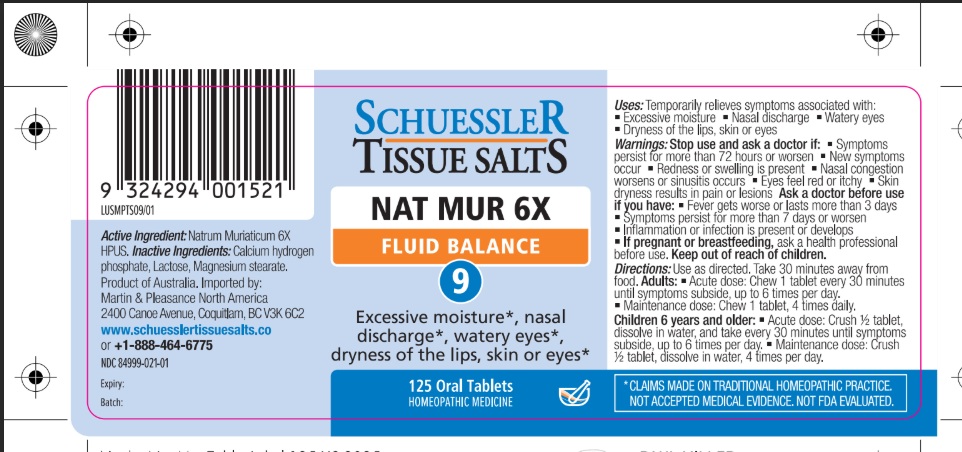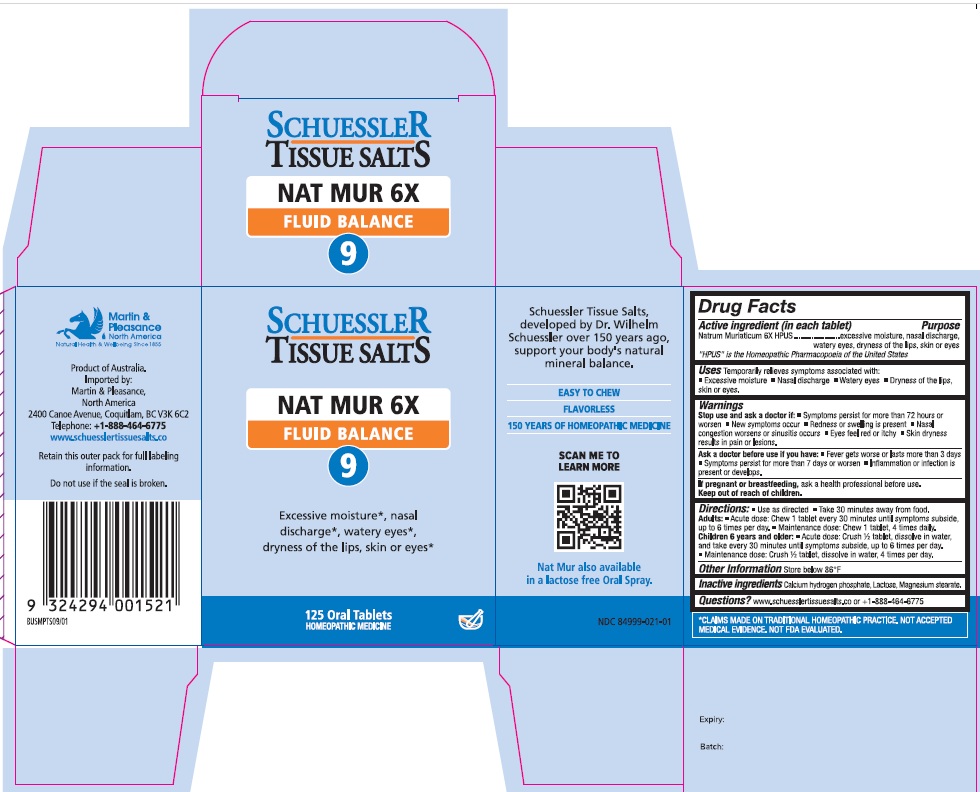 DRUG LABEL: Schuessler Tissue Salts Nat Mur Fluid Balance 9
NDC: 84999-021 | Form: TABLET, CHEWABLE
Manufacturer: Martin & Pleasance Pty Ltd
Category: homeopathic | Type: HUMAN OTC DRUG LABEL
Date: 20250804

ACTIVE INGREDIENTS: SODIUM CHLORIDE 6 [hp_X]/1 1
INACTIVE INGREDIENTS: LACTOSE MONOHYDRATE; MAGNESIUM STEARATE; ANHYDROUS DIBASIC CALCIUM PHOSPHATE

Active Ingredients Purpose

Natrum Muriaticum 6X HPUS excessive moisture, nasal discharge, watery eyes, dryness of the lips, skin, or eyes

" HPUS" is the Homeopathic Pharmacopoeia of the United States

Uses

Temporarily relieves symptoms associated with

- Excessive moisture
- Nasal discharge
- Watery eyes
- Dryness of the lips, skin, or eyes

Warnings

Stop use and ask a doctor if:

- Symptoms persist for more than 72 hours or worsen
- New symptoms occur
- Redness or swelling is present
- Nasal congestion worsens or sinusitis occurs
- Eyes feel red or itchy
- Skin dryness results in pain or lesions

If pregnant or breastfeeding: Ask a health professional before use.

Ask a doctor before use if you have:
• Fever get worse or lasts more than 3 days
• Symptoms persist for more than 7 days or worsen
• Inflammation or inflection is present or develops.

Keep out of reach of children.

Directions

- Use as directed
- Take 30 minutes away from food

Adults: Acute dose: Chew 1 tablet every 30 minutes until symptoms subside up to 6 times per day.

Maintenance dose: Chew 1 tablet, 4 times daily.

Children 6 years and older: Acute dose: Crush 1/2 tablet, dissolve in water, and take every 30 minutes until symptoms subside, up to six times per day.

Maintenance dose :Crush 1/2 tablet, dissolve in water, 4 times per day.

Other Information

Store below 86°F

Inactive Ingredients

Calcium hydrogen phosphate, Lactose, Magnesium stearate

Questions?www.schuesslertissuesalts.co or + 1-888-464-6775